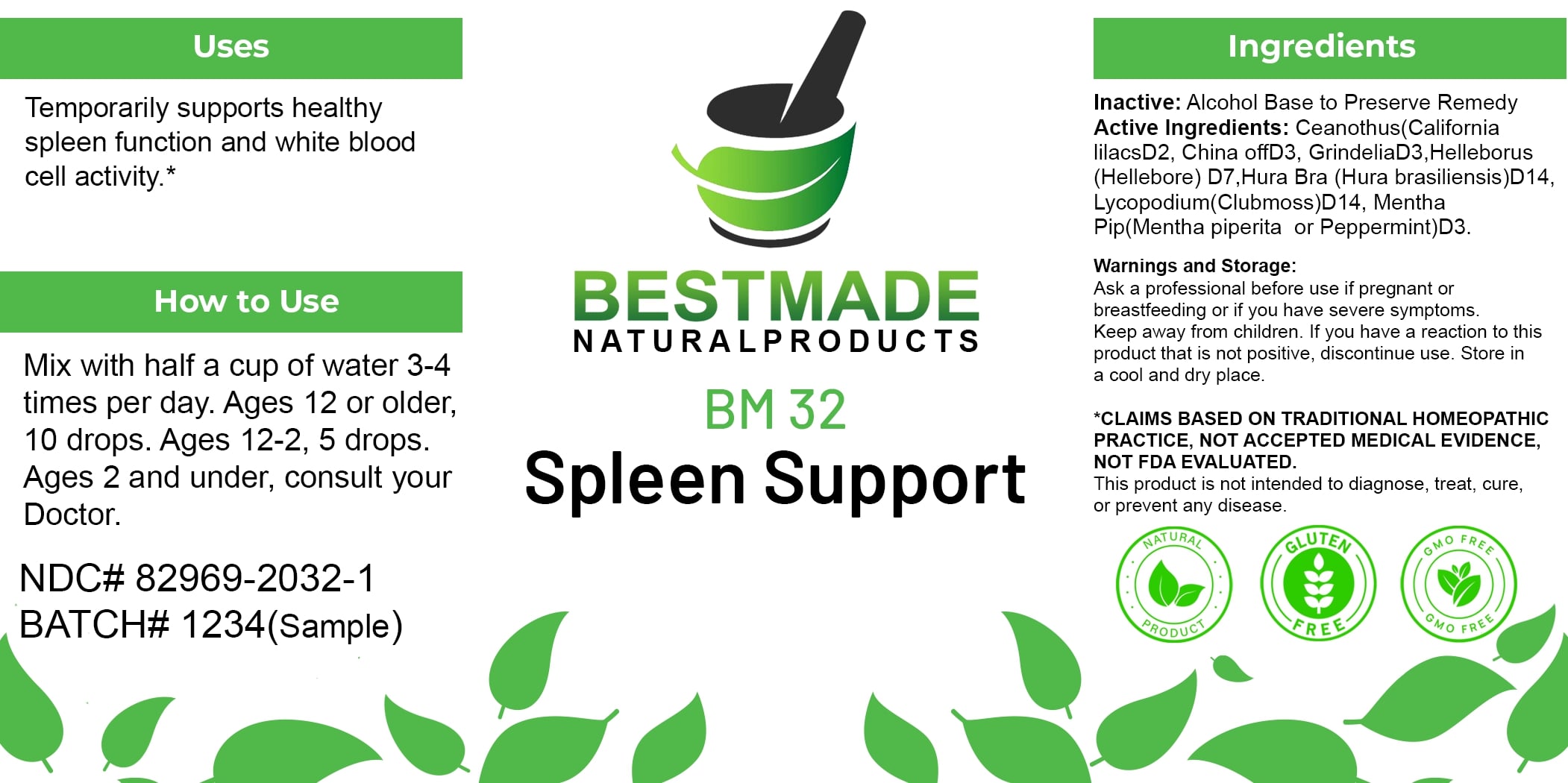 DRUG LABEL: Bestmade Natural Products BM32
NDC: 82969-2032 | Form: LIQUID
Manufacturer: Bestmade Natural Products
Category: homeopathic | Type: HUMAN OTC DRUG LABEL
Date: 20250123

ACTIVE INGREDIENTS: CINCHONA OFFICINALIS BARK 30 [hp_C]/30 [hp_C]; HELLEBORUS NIGER ROOT 30 [hp_C]/30 [hp_C]; HURA CREPITANS SAP 30 [hp_C]/30 [hp_C]; GRINDELIA SQUARROSA FLOWERING TOP 30 [hp_C]/30 [hp_C]; LYCOPODIUM CLAVATUM SPORE 30 [hp_C]/30 [hp_C]; MENTHA PIPERITA 30 [hp_C]/30 [hp_C]; CEANOTHUS AMERICANUS LEAF 30 [hp_C]/30 [hp_C]
INACTIVE INGREDIENTS: ALCOHOL 30 [hp_C]/30 [hp_C]

BM32

DOSAGE AND ADMINISTRATION

How to Use

Mix with half a cup of water 3-4 times per day. Ages 12 or older, 10 drops. Ages 12-2, 5 drops. Ages 2 and under, consult your Doctor.

INACTIVE INGREDIENT

Ingredients

Inactive: Alcohol Base to Preserve Remedy

Uses

Temporarily supports healthy spleen function and white blood cell activity.*

*CLAIMS BASED ON TRADITIONAL HOMEOPATHIC PRACTICE, NOT ACCEPTED MEDICAL EVIDENCE, NOT FDA EVALUATED.

This product is not intended to diagnose, treat, cure, or prevent any disease.

Uses

Temporarily supports healthy spleen function and white blood cell activity.*

*CLAIMS BASED ON TRADITIONAL HOMEOPATHIC PRACTICE, NOT ACCEPTED MEDICAL EVIDENCE, NOT FDA EVALUATED.

This product is not intended to diagnose, treat, cure, or prevent any disease.

ACTIVE INGREDIENT

Active Ingredients: Ceanothus(California lilacs)D2, China off D3, Grindelia D3, Helleborus (Hellebore) D7, Hura Bra (Hura brasiliensis) D14, Lycopodium (Clubmoss) D14, Mentha Pip (Mentha piperita or Peppermint) D3.

KEEP OUT OF REACH OF CHILDREN

Warnings and Storage:

Ask a professional before use if pregnant or breastfeeding or if you have severe symptoms. Keep away from children. If you have a reaction to this product that is not positive, discontinue use. Store in a cool and dry place.

Warnings and Storage:

Ask a professional before use if pregnant or breastfeeding or if you have severe symptoms. Keep away from children. If you have a reaction to this product that is not positive, discontinue use. Store in a cool and dry place.

*CLAIMS BASED ON TRADITIONAL HOMEOPATHIC PRACTICE, NOT ACCEPTED MEDICAL EVIDENCE, NOT FDA EVALUATED.

This product is not intended to diagnose, treat, cure, or prevent any disease.

Entire package label